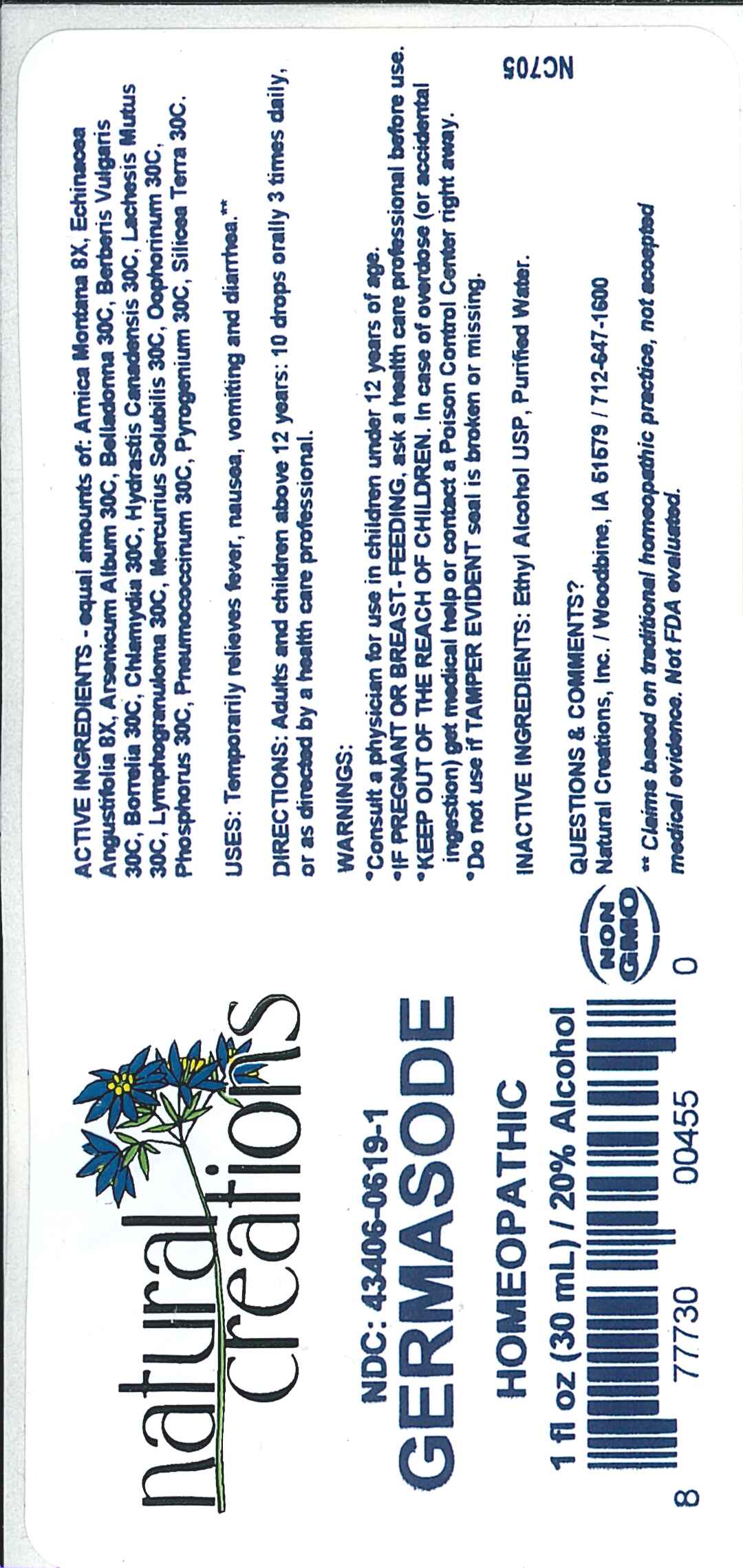 DRUG LABEL: Germasode
NDC: 43406-0619 | Form: LIQUID
Manufacturer: Natural Creations, Inc
Category: homeopathic | Type: HUMAN OTC DRUG LABEL
Date: 20251212

ACTIVE INGREDIENTS: ARNICA MONTANA WHOLE 8 [hp_X]/1 mL; ECHINACEA ANGUSTIFOLIA WHOLE 8 [hp_X]/1 mL; ARSENIC TRIOXIDE 30 [hp_C]/1 mL; ATROPA BELLADONNA 30 [hp_C]/1 mL; BERBERIS VULGARIS ROOT BARK 30 [hp_C]/1 mL; BORRELIA BURGDORFERI 30 [hp_C]/1 mL; CHLAMYDIA TRACHOMATIS 30 [hp_C]/1 mL; GOLDENSEAL 30 [hp_C]/1 mL; LACHESIS MUTA VENOM 30 [hp_C]/1 mL; MERCURIUS SOLUBILIS 30 [hp_C]/1 mL; SUS SCROFA OVARY 30 [hp_C]/1 mL; PHOSPHORUS 30 [hp_C]/1 mL; RANCID BEEF 30 [hp_C]/1 mL; SILICON DIOXIDE 30 [hp_C]/1 mL
INACTIVE INGREDIENTS: ALCOHOL; WATER

Germasode

ACTIVE INGREDIENT

ACTIVE INGREDIENTS - equal amounts of: Arnica Montana 8X, Echinacea Angustifolia 8X, Arsenicum Album 30C, Belladonna 30C, Berberis Vulgaris 30C, Borrelia 30C, Chlamydia 30C, Hydrastis Canadensis 30C, Lachesis Mutus 30C, Lymphogranuloma 30C, Mercurius Solubilis 30C, Oophorinum 30C, Phosphorus 30C, Pneumococcinum 30C, Pyrogenium 30C, Silicea Terra 30C

INDICATIONS AND USAGE

USES: Temporarily relieves fever, nausea, vomiting and diarrhea.**

PURPOSE

USES: Temporarily relieves fever, nausea, vomiting and diarrhea.**

DOSAGE AND ADMINISTRATION

DIRECTIONS: Adults & children above 12 years: 10 drops orally 3 times daily, or as directed by a health care professional.

KEEP OUT OF REACH OF CHILDREN

KEEP OUT OF THE REACH OF CHILDREN. In case of overdose (or accidental ingestion) get medical help or contact a Poison Control Center right away.

WARNINGS:

- Consult a physician for use in children under 12 years of age.
- IF PREGNANT OR BREAST-FEEDING, ask a health care professional before use.
- KEEP OUT OF THE REACH OF CHILDREN. In case of overdose (or accidental ingestion) get medical help or contact a Poison Control Center right away.
- Do not use if TAMPER EVIDENT seal is broken or missing.

INACTIVE INGREDIENTS: Ethyl Alcohol USP, Purified Water

QUESTIONS & COMMENTS?

Natural Creations, Inc. / Woodbine, IA 51579 / 712-647-1600

REFERENCES

**Claims based on traditional homeopathic practice, not accepted medical evidence. Not FDA evaluated.

PACKAGE LABEL

NDC:43406-0619-1

Germasode

HOMEOPATHIC

1 fl oz (30mL) / 20% Alcohol